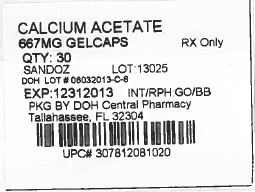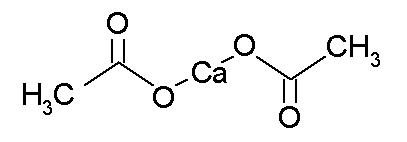 DRUG LABEL: Calcium Acetate
NDC: 53808-0905 | Form: CAPSULE
Manufacturer: State of Florida DOH Central Pharmacy
Category: prescription | Type: HUMAN PRESCRIPTION DRUG LABEL
Date: 20140227

ACTIVE INGREDIENTS: CALCIUM ACETATE 667 mg/1 1

HIGHLIGHTS OF PRESCRIBING INFORMATION

These highlights do not include all the information needed to use calcium acetate gelcaps safely and effectively. See full prescribing information for calcium acetate gelcaps.
Calcium Acetate Gelcaps (calcium acetate): 667 mg
Initial U.S. Approval: 1990

1 INDICATIONS AND USAGE

- Calcium Acetate is a phosphate binder indicated for the reduction of serum phosphorus in patients with end stage renal disease. (1)

2 DOSAGE AND ADMINISTRATION

- Starting dose is 2 gelcaps with each meal. (2)
- Titrate the dose every 2-3 weeks until acceptable serum phosphorus level is reached. Most patients require 3-4 gelcaps with each meal. (2)

3 DOSAGE FORMS AND STRENGTHS

- Capsule: 667 mg calcium acetate gelcap. (3)

4 CONTRAINDICATIONS

- Hypercalcemia. (4)

WARNINGS AND PRECAUTIONS

- Treat mild hypercalcemia by reducing or interrupting calcium acetate and Vitamin D. Severe hypercalcemia may require hemodialysis and discontinuation of calcium acetate. (5.1)
- Hypercalcemia may aggravate digitalis toxicity. (5.2)

6 ADVERSE REACTIONS

- The most common (> 10%) adverse reactions are hypercalcemia, nausea and vomiting. (6.1)
- In clinical studies, patients have occasionally experienced nausea during calcium acetate therapy. (6)

To report SUSPECTED ADVERSE REACTIONS, contact Fresenius Medical Care North America at 1-800-323-5188 or FDA at 1-800-FDA-1088 or www.fda.gov/medwatch

7 DRUG INTERACTIONS

- Calcium acetate may decrease the bioavailability of tetracyclines or fluoroquinolones. (7)
- When clinically significant drug interactions are expected, administer the drug at least one hour before or at least three hours after calcium acetate or consider monitoring blood levels of the drug. (7)

FULL PRESCRIBING INFORMATION

1 INDICATIONS AND USAGE

Calcium Acetate Gelcaps is a phosphate binder indicated to reduce serum phosphorus in patients with end stage renal disease (ESRD).

2 DOSAGE AND ADMINISTRATION

The recommended initial dose of calcium acetate for the adult dialysis patient is 2 gelcaps with each meal. Increase the dose gradually to lower serum phosphorus levels to the target range, as long as hypercalcemia does not develop. Most patients require 3-4 gelcaps with each meal.

3 DOSAGE FORMS AND STRENGTHS

Capsule: 667 mg calcium acetate per gelcap.

4 CONTRAINDICATIONS

Patients with hypercalcemia.

WARNINGS AND PRECAUTIONS

5.1 Hypercalcemia

Patients with end stage renal disease may develop hypercalcemia when treated with calcium, including calcium acetate. Avoid the use of calcium supplements, including calcium-based nonprescription antacids, concurrently with calcium acetate.

An overdose of calcium acetate may lead to progressive hypercalcemia, which may require emergency measures. Therefore, early in the treatment phase during the dosage adjustment period, monitor serum calcium levels twice weekly. Should hypercalcemia develop, reduce the calcium acetate dosage, or discontinue the treatment, depending on the severity of hypercalcemia.

More severe hypercalcemia (Ca >12 mg/dL) is associated with confusion, delirium, stupor and coma. Severe hypercalcemia can be treated by acute hemodialysis and discontinuing calcium acetate therapy.

Mild hypercalcemia (10.5 to 11.9 mg/dL) may be asymptomatic or manifest as constipation, anorexia, nausea, and vomiting. Mild hypercalcemia is usually controlled by reducing the calcium acetate dose or temporarily discontinuing therapy. Decreasing or discontinuing Vitamin D therapy is recommended as well.

Chronic hypercalcemia may lead to vascular calcification and other soft-tissue calcification. Radiographic evaluation of suspected anatomical regions may be helpful in early detection of soft tissue calcification. The long term effect of calcium acetate on the progression of vascular or soft tissue calcification has not been determined.

Hypercalcemia (>11 mg/dL) was reported in 16% of patients in a 3-month study of solid dose formulation of calcium acetate; all cases resolved upon lowering the dose or discontinuing treatment.

Maintain the serum calcium-phosphorus (Ca x P) product below 55 mg^2/dL^2.

5.2 Concomitant Use with Medications

Hypercalcemia may aggravate digitalis toxicity.

6 ADVERSE REACTIONS

Hypercalcemia is discussed elsewhere [see Warnings and Precautions (5.1)]

6.1 Clinical Trials Experience

Because clinical trials are conducted under widely varying conditions, adverse reaction rates observed in the clinical trials of a drug cannot be directly compared to rates in the clinical trials of another drug and may not reflect the rates observed in practice.

In clinical studies, calcium acetate has been generally well tolerated.

Calcium acetate was studied in a 3-month, open-label, non-randomized study of 98 enrolled ESRD hemodialysis patients and in a two week double-blind, placebo-controlled, cross-over study with 69 enrolled ESRD hemodialysis patients. Adverse reactions (>2% on treatment) from these trials are presented in Table 1.

Table 1: Adverse Reactions in Patients with End-Stage Renal Disease Undergoing Hemodialysis
Preferred Term | Total adverse reactions reported for calcium acetate n=167 n (%) | 3-mo, open-label study of calcium acetate n=98 n (%) | Double blind, placebo-controlled, cross-over study of calcium acetate n=69
Preferred Term | Total adverse reactions reported for calcium acetate n=167 n (%) | 3-mo, open-label study of calcium acetate n=98 n (%) | Calcium acetate n (%) | Placebo n (%)
Nausea | 6 (3.6) | 6 (6.1) | 0 (0.0) | 0 (0.0)
Vomiting | 4 (2.4) | 4 (4.1) | 0 (0.0) | 0 (0.0)
Hypercalcemia | 21 (12.6) | 16 (16.3) | 5 (7.2) | 0 (0.0)

Mild hypercalcemia may be asymptomatic or manifest itself as constipation, anorexia, nausea, and vomiting. More severe hypercalcemia is associated with confusion, delirium, stupor, and coma. Decreasing dialysate calcium concentration could reduce the incidence and severity of calcium acetate-induced hypercalcemia. Isolated cases pruritus have been reported, which may represent allergic reactions.

6.2 Postmarketing Experience

Because these reactions are reported voluntarily from a population of uncertain size, it is not always possible to estimate their frequency or to establish a causal relationship to drug exposure.

The following additional adverse reactions have been identified during post-approval of calcium acetate: dizziness, edema, and weakness.

7 DRUG INTERACTIONS

The drug interaction of calcium acetate is characterized by the potential of calcium to bind to drugs with anionic functions (e.g., carboxyl, and hydroxyl groups). Calcium acetate may decrease the bioavailability of tetracyclines or fluoroquinolones via this mechanism.

There are no empirical data on avoiding drug interactions between calcium acetate and most concomitant drugs. When administering an oral medication with calcium acetate where a reduction in the bioavailability of that medication would have a clinically significant effect on its safety or efficacy, administer the drug one hour before or three hours after calcium acetate. Monitor blood levels of the concomitant drugs that have a narrow therapeutic range. Patients taking anti-arrhythmic medications for the control of arrhythmias and anti-seizure medications for the control of seizure disorders were excluded from the clinical trials with all forms of calcium acetate.

7.1 Ciprofloxacin

In a study of 15 healthy subjects, a co-administered single dose of 4 calcium acetate tablets, approximately 2.7 g, decreased the bioavailability of ciprofloxacin by approximately 50%.

8 USE IN SPECIFIC POPULATIONS

8.1 Pregnancy

Pregnancy Category C
Calcium acetate gelcaps contains calcium acetate. Animal reproduction studies have not been conducted with calcium acetate, and there are no adequate and well controlled studies of calcium acetate use in pregnant women. Patients with end stage renal disease may develop hypercalcemia with calcium acetate treatment [see Warnings and Precautions (5.1)]. Maintenance of normal serum calcium levels is important for maternal and fetal well being. Hypercalcemia during pregnancy may increase the risk for maternal and neonatal complications such as stillbirth, preterm delivery, and neonatal hypocalcemia and hypoparathyroidism. Calcium acetate treatment, as recommended, is not expected to harm a fetus if maternal calcium levels are properly monitored during and following treatment.

8.2 Labor and Delivery

The effects of calcium acetate on labor and delivery are unknown.

8.3 Nursing Mothers

Calcium acetate is excreted in human milk. Human milk feeding by a mother receiving calcium acetate is not expected to harm an infant, provided maternal serum calcium levels are appropriately monitored.

8.4 Pediatric Use

Safety and effectiveness in pediatric patients have not been established.

8.5 Geriatric Use

Clinical studies of calcium acetate did not include sufficient numbers of subjects aged 65 and over to determine whether they respond differently from younger subjects. Other clinical experience has not identified differences in responses between elderly and younger patients. In general, dose selection for an elderly patient should be cautious, usually starting at the low end of the dosing range, reflecting the greater frequency of decreased hepatic, renal, or cardiac function, and of concomitant disease or other drug therapy.

10 OVERDOSAGE

Administration of calcium acetate in excess of the appropriate daily dosage may result in hypercalcemia [see Warnings and Precautions (5.1)].

11 DESCRIPTION

Calcium acetate acts as a phosphate binder. Its chemical name is calcium acetate. Its molecular formula is C4H6CaO4, and its molecular weight is 158.17. Its structural formula is:

Each opaque gelcap with a blue cap and white body is spin printed in blue and white ink with “SANDOZ" printed on the cap and “576” printed on the body. Each gelcap contains 667 mg calcium acetate, USP (anhydrous; Ca(CH3COO)2; MW=158.17 grams) equal to 169 mg (8.45 mEq) calcium, and 10 mg of the inert binder, polyethylene glycol 8000 NF. The gelatin cap and body have the following inactive ingredients: FD&C blue #1, D&C red #28, titanium dioxide, USP and gelatin, USP.

12 CLINICAL PHARMACOLOGY

Patients with ESRD retain phosphorus and can develop hyperphosphatemia. High serum phosphorus can precipitate serum calcium resulting in ectopic calcification. Hyperphosphatemia also plays a role in the development of secondary hyperparathyroidism in patients with ESRD.

12.1 Mechanism of Action

Calcium acetate, when taken with meals, combines with dietary phosphate to form an insoluble calcium phosphate complex, which is excreted in the feces, resulting in decreased serum phosphorus concentration.

12.2 Pharmacodynamics

Orally administered calcium acetate from pharmaceutical dosage forms is systemically absorbed up to approximately 40% under fasting conditions and up to approximately 30% under non-fasting conditions. This range represents data from both healthy subjects and renal dialysis patients under various conditions.

13 NONCLINICAL TOXICOLOGY

13.1 Carcinogenesis, Mutagenesis, Impairment of Fertility

No carcinogenicity, mutagenicity, or fertility studies have been conducted with calcium acetate.

14 CLINICAL STUDIES

Effectiveness of calcium acetate in decreasing serum phosphorus has been demonstrated in two studies of the calcium acetate solid oral dosage form.

Ninety-one patients with end-stage renal disease who were undergoing hemodialysis and were hyperphosphatemic (serum phosphorus >5.5 mg/dL) following a 1-week phosphate binder washout period contributed efficacy data to an open-label, non-randomized study.

The patients received calcium acetate 667 mg tablets at each meal for a period of 12 weeks. The initial starting dose was 2 tablets per meal for 3 meals a day, and the dose was adjusted as necessary to control serum phosphorus levels. The average final dose after 12 weeks of treatment was 3.4 tablets per meal. Although there was a decrease in serum phosphorus, in the absence of a control group the true magnitude of effect is uncertain.

The data presented in Table 2 demonstrate the efficacy of calcium acetate in the treatment of hyperphosphatemia in end-stage renal disease patients. The effects on serum calcium levels are also presented.

Table 2: Average Serum Phosphorous and Calcium Levels at Pre-Study, Interim, and Study Completion Time points
Parameter | Pre-Study | Week 4 b | Week 8 | Week 12 | p-valuec
Phosphorus (mg/dL)a | 7.4 ± 0.17 | 5.9 ± 0.16 | 5.6 ± 0.17 | 5.2 ± 0.17 | ≤0.01
Calcium (mg/dL)a | 8.9 ± 0.09 | 9.5 ± 0.10 | 9.7 ± 0.10 | 9.7 ± 0.10 | ≤0.01
aValues expressed as mean ± SE.
bNinety-one patients completed at least 6 weeks of the study.
cANOVA of difference in values at pre-study and study completion.

There was a 30% decrease in serum phosphorus levels during the 12 week study period (p<0.01). Two-thirds of the decline occurred in the first month of the study. Serum calcium increased 9% during the study mostly in the first month of the study.

Treatment with the phosphate binder was discontinued for patients from the open-label study, and those patients whose serum phosphorus exceeded 5.5 mg/dL were eligible for entry into a double-blind, placebo-controlled, cross-over study. Patients were randomized to receive calcium acetate or placebo, and each continued to receive the same number of tablets as had been individually established during the previous study. Following 2 weeks of treatment, patients switched to the alternative therapy for an additional 2 weeks.

The phosphate binding effect of calcium acetate is shown in the Table 3.

Table 3: Serum Phosphorous and Calcium Levels at Study Initiation and After Completion of Each Treatment Arm
Parameter | Pre-Study | Post-Treatment |  | p-valueb
Parameter | Pre-Study | Calcium Acetate | Placebo
Phosphorus (mg/dL)a | 7.3 ± 0.18 | 5.9 ± 0.24 | 7.8 ± 0.22 | <0.01
Calcium (mg/dL)a | 8.9 ± 0.11 | 9.5 ± 0.13 | 8.8 ± 0.12 | <0.01
aValues expressed as mean ± SEM
bANOVA of calcium acetate vs. placebo after 2 weeks of treatment.

Overall, 2 weeks of treatment with calcium acetate statistically significantly (p<0.01) decreased serum phosphorus by a mean of 19% and increased serum calcium by a statistically significant (p<0.01) but clinically unimportant mean of 7%.

16 HOW SUPPLIED/STORAGE AND HANDLING

Gelcap A white and blue gelcap for oral administration containing 667 mg calcium acetate (anhydrous Ca(CH3COO)2; MW=158.17 grams) equal to 169 mg (8.45 mEq) calcium.

They are supplied by State of Florida DOH Central Pharmacy as follows:

NDC | Strength | Quantity/Form | Color | Source Prod. Code
53808-0905-1 | 667 MG | 30 Capsules in a Blister Pack | BLUE | 0781-2081

STORAGE AND HANDLING

STORAGE: Store at 25°C (77°F); excursions permitted to 15-30°C (59- 86°F) [See USP "Controlled Room Temperature"].

17 PATIENT COUNSELING INFORMATION

Inform patients to take calcium acetate with meals, adhere to their prescribed diets, and avoid the use of calcium supplements including nonprescription antacids. Inform the patients about the symptoms of hypercalcemia [see Warnings and Precautions (5.1) and Adverse Reactions (6.1)].

Advise patients who are taking an oral medication where reduction in the bioavailability of that medication would have clinically significant effect on its safety or efficacy to take the drug one hour before or three hours after calcium acetate.

Manufactured for
Fresenius Medical Care North America
Waltham, MA 02451
1-800-323-5188

Distributed by
Sandoz Inc.
Princeton, NJ 08540

This Product was Repackaged By:

State of Florida DOH Central Pharmacy
104-2 Hamilton Park Drive
Tallahassee, FL 32304
USA

PACKAGE LABEL

Label Image for 53808-0905
667mg